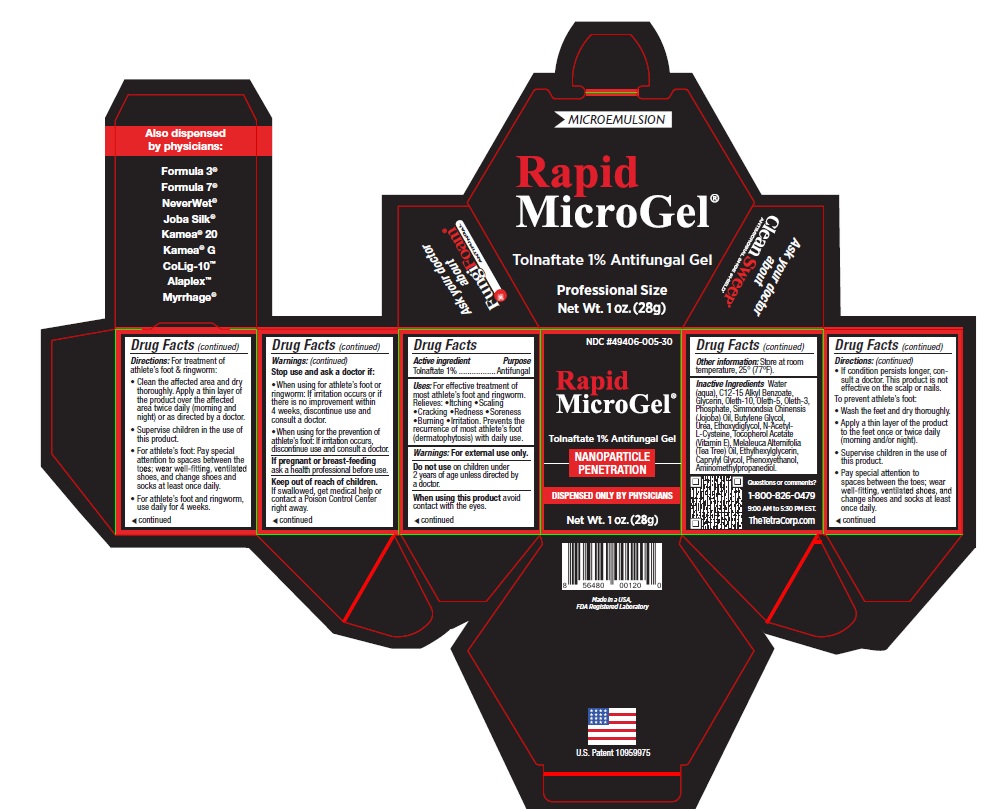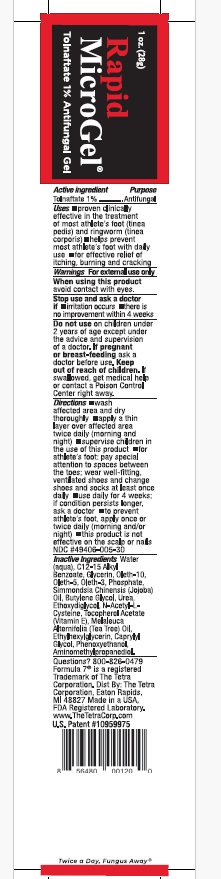 DRUG LABEL: Rapid MicroGel
NDC: 49406-005 | Form: GEL
Manufacturer: The Tetra Corporation
Category: otc | Type: HUMAN OTC DRUG LABEL
Date: 20250819

ACTIVE INGREDIENTS: TOLNAFTATE 1 g/100 g
INACTIVE INGREDIENTS: WATER; JOJOBA OIL; GLYCERIN; OLETH-10; OLETH-3 PHOSPHATE; OLETH-5; PEG-20 HYDROGENATED LANOLIN; BUTYLENE GLYCOL; UREA; ALKYL (C12-15) BENZOATE; .ALPHA.-TOCOPHEROL ACETATE; TEA TREE OIL; ETHYLHEXYLGLYCERIN; CAPRYLYL GLYCOL; PHENOXYETHANOL; ACETYLCYSTEINE; AMINOMETHYLPROPANOL; SODIUM CHLORIDE

Uses:

Antifungal

INDICATIONS AND USAGE

For effective treatment of most athlete’s foot and ringworm.
Relieves:

• Itching

• Scaling

• Cracking
• Redness

• Soreness

• Burning

• Irritation

Prevents the recurrence of most athlete’s foot (dermatophytosis) with daily use.

Active ingredient

Tolnaftate 1%

Stop use and ask a doctor if:

• When using for treatment of athlete’s foot or ringworm: If irritation occurs or if there is no improvement within 4 weeks, discontinue use and consult a doctor.

• When using for the prevention of athlete’s foot: If irritation occurs, discontinue use and consult a doctor.

DO NOT USE SECTION

Do not useon children under 2 years of age unless directed by a doctor.

PREGNANCY OR BREAST FEEDING

If pregnant or breast-feedingask a health professional before use.

Questions or comments?

1-800-826-0479
9:00 AM to 5:30 PM EST.

Inactive Ingredients

Inactive Ingredients: Water (aqua),C12-15 Alkyl Benzoate, SimmondsiaChinensis (Jojoba) Oil, Glycerin,Oleth-10, Oleth-5, Oleth-3 Phosphate,PEG-20 Hydrogenated Lanolin,Butylene Glycol, Urea, Ethoxydiglycol,N-Acetyl-L-Cysteine, TocopherolAcetate (Vitamin E), Melaleuca
Alternifolia (Tea Tree) Oil, DisodiumEDTA, Ethylhexylglycerin, CaprylylGlycol, Phenoxyethanol, Aminomethylpropanediol,Sodium Chloride.

Directions:

For treatment of athlete’s foot and ringworm:

• Clean the affected area and dry thoroughly. Apply a thin layer of the product over the affected area twice daily (morning and night) or as
directed by a doctor.
• Supervise children in the use of this product.
• For athlete’s foot: Pay special attention to spaces between the toes; wear well-fitting, ventilated shoes, and change shoes and socks
at least once daily.
• For athlete’s foot and ringworm, use daily for 4 weeks.
• If condition persists longer, consult a doctor. This product is not effective on the scalp or nails.

To prevent athlete’s foot:
• Wash the feet and dry thoroughly.
• Apply a thin layer of the product to the feet once or twice daily (morning and/or night).
• Supervise children in the use of this product.
• Pay special attention to spaces between the toes; wear well-fitting,ventilated shoes, and change shoes and socks at least once daily.

Other information

Store at room temperature, 25ºC (77ºF).

Warnings

For external use only. When using this product avoid contact with eyes.

Keep out of reach of children. If swallowed, get medical help or contact a Poison Control Center right away.